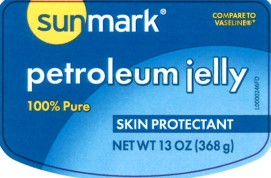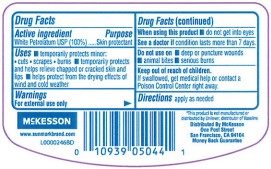 DRUG LABEL: Petroleum
NDC: 70677-0120 | Form: JELLY
Manufacturer: Strategic Sourcing Services LLC
Category: otc | Type: HUMAN OTC DRUG LABEL
Date: 20260217

ACTIVE INGREDIENTS: PETROLATUM 1 g/1 g

SunMark 069.001/069AA
Petroleum Jelly

Active ingredient

White petrolatum USP (100%)

purpose

Skin Protectant

Uses

- temporarily protects monor: cuts - scrapes - burns
- temporarily protects and helps relieve chapped or cracked skin and lips
- helps protect from the drying effects of wind and cold weather

Warnings

For external use only

When using this product

- do not get into eyes

See a doctor if

condition lasts more than 7 days

do not use on

- deep or puncture wounds
- animal bites
- serious burns

Keep out of reach of children.

If swallowed, get medical help or contact a Poison Control Center right away.

Directions

apply as needed

inactive ingredients

None

Disclaimer

*This product is not manufactured or distributed by Unilever, distributor of Vaseline.

Adverse Reactions

Distributed by McKesson

One Post Street

San Francisco, CA 94104

Money Back Guarantee

McKesson

www.sunmarkbrand.com

Principal display panel

COMPARE TO VASELINE®*

SUNMARK®

petroleum jelly

100% Pure

SKIN PROTECTANT

NET WT 13 OZ (368 g)